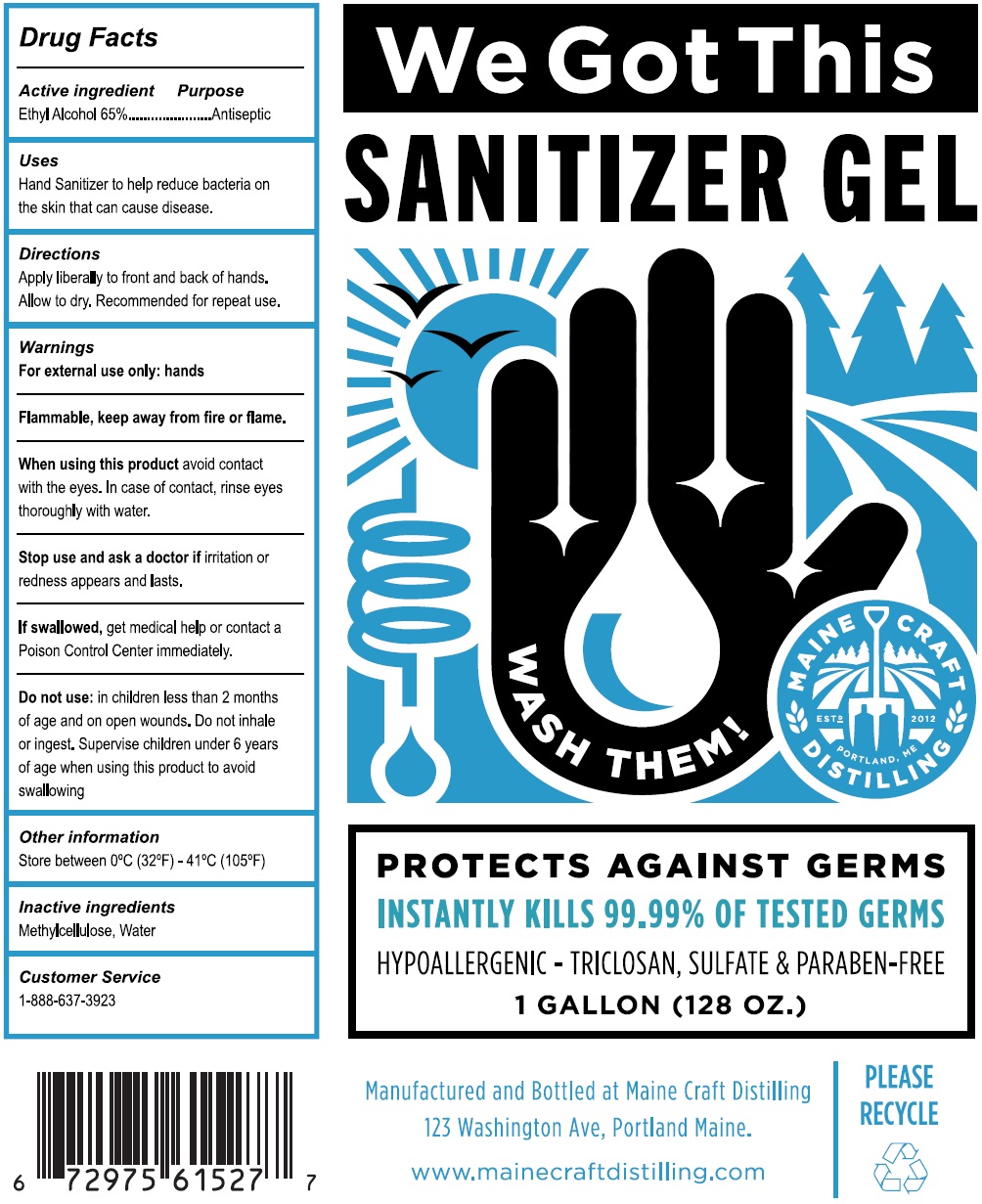 DRUG LABEL: We Got This Sanitizer
NDC: 79359-900 | Form: GEL
Manufacturer: Maine Craft Distilling, LLC
Category: otc | Type: HUMAN OTC DRUG LABEL
Date: 20200901

ACTIVE INGREDIENTS: ALCOHOL 65 mL/100 mL
INACTIVE INGREDIENTS: METHYLCELLULOSE, UNSPECIFIED; WATER

We Got This SANITIZER GEL

Active ingredient

Ethyl Alcohol 65%

Purpose

Antiseptic

Uses

Hand Sanitizer to help reduce bacteria on the skin that can cause disease.

Directions

Apply liberally to front and back of hands.

Allow to dry. Recommended for repeat use.

Warnings

For external use only: hands

Flammable, keep away from fire or flame.

When using this product avoid contact with the eyes. In case of contact, rinse eyes thoroughly with water.

Stop use and ask a doctor if irritation or redness appears and lasts.

Do not use: in children less than 2 months of age and on open wounds. Do not inhale or ingest.

Supervise children under 6 years of age when using this product to avoid swallowing

KEEP OUT OF REACH OF CHILDREN

If swallowed, get medical help or contact a Poison Control Center immediately.

Other information

Store between 0ºC (32ºF) - 41ºC (105ºF)

Inactive ingredients

Methylcellulose, Water

Customer Service

1-888-637-3923

WASH THEM!

PROTECTS AGAINST GERMS

INSTANTLY KILLS 99.99% OF TESTED GERMS

HYPOALLERGENIC - TRICLOSAN, SULFATE & PARABEN-FREE

Manufactured and Bottled at Maine Craft Distilling

123 Washington Ave, Portland Maine.

www.mainecraftdistilling.com

PLEASE RECYCLE